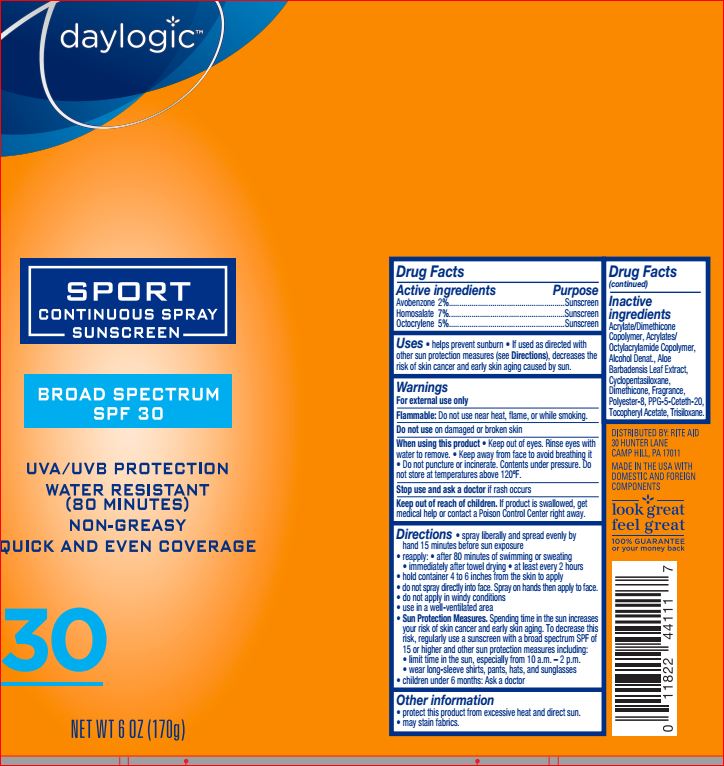 DRUG LABEL: Sport Sunscreen SPF 30
NDC: 11822-2224 | Form: SPRAY
Manufacturer: Rite Aid
Category: otc | Type: HUMAN OTC DRUG LABEL
Date: 20180525

ACTIVE INGREDIENTS: Avobenzone 2 g/100 g; Homosalate 7 g/100 g; Octocrylene 5 g/100 g
INACTIVE INGREDIENTS: ALCOHOL; ALOE; CYCLOMETHICONE 5; Dimethicone; POLYESTER-8 (1400 MW, CYANODIPHENYLPROPENOYL CAPPED); PPG-5-Ceteth-20; .ALPHA.-TOCOPHEROL ACETATE; Trisiloxane

Drug Facts

Active ingredients Purpose

Avobenzone -2.0%
Homosalate - 7.00%
Octocrylene - 5.00% Sunscreen

INDICATIONS AND USAGE

- helps prevent sunburn
- if used as directed with other sun protection messures (see Directions) decreases the risk of skin cancer and early skin aging caused by sun.

Warnings

For external use only
Do not use on damaged or broken skin
When using this product keep out of eyes. Rinse with water to remove.
Stop use and ask a doctor if rash occurs
Keep out of reach of children. If product is swallowed, get medical help or contact a Poison Control Center right away.

Directions

spray liberally and spread evenly by hand 15 minutes before sun exposure
• reapply: • after 80 minutes of swimming or sweating
• immediately after towel drying • at least every 2 hours
• Sun Protection Measures. Spending time in the sun
increases your risk of skin cancer and early skin aging.
To decrease this risk, regularly use a sunscreen with a
broad spectrum SPF of 15 or higher and other sun
protection measures including:
• limit time in the sun, especially from 10 a.m. – 2 p.m.
• wear long-sleeve shirts, pants, hats, and sunglasses
• children under 6 months: Ask a doctor

Inactive ingredients

Acrylates/Dimethicone Copolymer
Acrylates/Octylacrylamide Copolymer
Alcohol Denat.
Aloe Barbadensis Leaf Extract
Cyclopentasiloxane
Dimethicone
Fragrance
Polyester-8
PPG-5-Ceteth-20
Tocopheryl Acetate
Trisiloxane